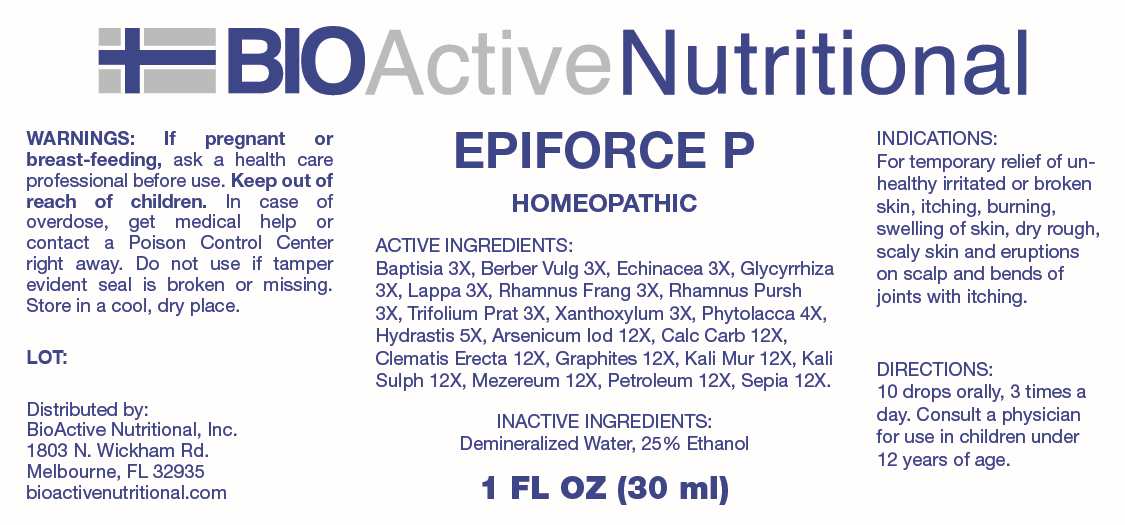 DRUG LABEL: Epiforce P
NDC: 43857-0645 | Form: LIQUID
Manufacturer: BioActive Nutritional, Inc.
Category: homeopathic | Type: HUMAN OTC DRUG LABEL
Date: 20241212

ACTIVE INGREDIENTS: BAPTISIA TINCTORIA ROOT 3 [hp_X]/1 mL; BERBERIS VULGARIS ROOT BARK 3 [hp_X]/1 mL; ECHINACEA ANGUSTIFOLIA WHOLE 3 [hp_X]/1 mL; GLYCYRRHIZA GLABRA 3 [hp_X]/1 mL; ARCTIUM LAPPA ROOT 3 [hp_X]/1 mL; FRANGULA ALNUS BARK 3 [hp_X]/1 mL; FRANGULA PURSHIANA BARK 3 [hp_X]/1 mL; TRIFOLIUM PRATENSE FLOWER 3 [hp_X]/1 mL; ZANTHOXYLUM AMERICANUM BARK 3 [hp_X]/1 mL; PHYTOLACCA AMERICANA ROOT 4 [hp_X]/1 mL; GOLDENSEAL 5 [hp_Q]/1 mL; ARSENIC TRIIODIDE 12 [hp_X]/1 mL; OYSTER SHELL CALCIUM CARBONATE, CRUDE 12 [hp_X]/1 mL; CLEMATIS RECTA FLOWERING TOP 12 [hp_X]/1 mL; GRAPHITE 12 [hp_X]/1 mL; POTASSIUM CHLORIDE 12 [hp_X]/1 mL; POTASSIUM SULFATE 12 [hp_X]/1 mL; DAPHNE MEZEREUM BARK 12 [hp_X]/1 mL; KEROSENE 12 [hp_X]/1 mL; SEPIA OFFICINALIS JUICE 12 [hp_X]/1 mL
INACTIVE INGREDIENTS: WATER; ALCOHOL

DRUG FACTS:

ACTIVE INGREDIENTS:

Baptisia Tinctoria 3X, Berberis Vulgaris 3X, Echinacea 3X, Glycyrrhiza Glabra 3X, Lappa Major 3X, Rhamnus Frangula 3X, Rhamnus Purshiana 3X, Trifolium Pratense 3X, Xanthoxylum Fraxineum 3X, Phytolacca Decandra 4X, Hydrastis Canadensis 5X, Arsenicum Iodatum 12X, Calcarea Carbonica 12X, Clematis Erecta 12X, Graphites 12X, Kali Muriaticum 12X, Kali Sulphuricum 12X, Mezereum 12X, Petroleum 12X, Sepia 12X.

PURPOSE:

For temporary relief of unhealthy irritated or broken skin, itching, burning, swelling of skin, dry ro9ugh, scaly skin and eruptions on scalp and bends of joints with itching.

WARNINGS:

If pregnant or breast-feeding, ask a health care professional before use.

Keep out of reach of children. In case of overdose, get medical help or contact a Poison Control Center right away.

Do not use if tamper evident seal is broken or missing.

Store in a cool, dry place.

KEEP OUT OF REACH OF CHILDREN:

In case of overdose, get medical help or contact a Poison Control Center right away.

DIRECTIONS:

10 drops orally, 3 times a day. Consult a physician for use in children under 12 years of age.

INDICATIONS:

For temporary relief of unhealthy irritated or broken skin, itching, burning, swelling of skin, dry ro9ugh, scaly skin and eruptions on scalp and bends of joints with itching.

INACTIVE INGREDIENTS:

Demineralized Water, 25% Ethanol

QUESTIONS:

Distributed by:

BioActive Nutritional, Inc.

1803 N. Wickham Rd.

Melbourne, FL 32935

bioactivenutritional.com

PACKAGE LABEL DISPLAY:

BIOActiveNutritional

EPIFORCE P

HOMEOPATHIC

1 FL OZ (30 ml)